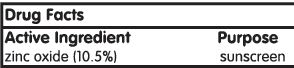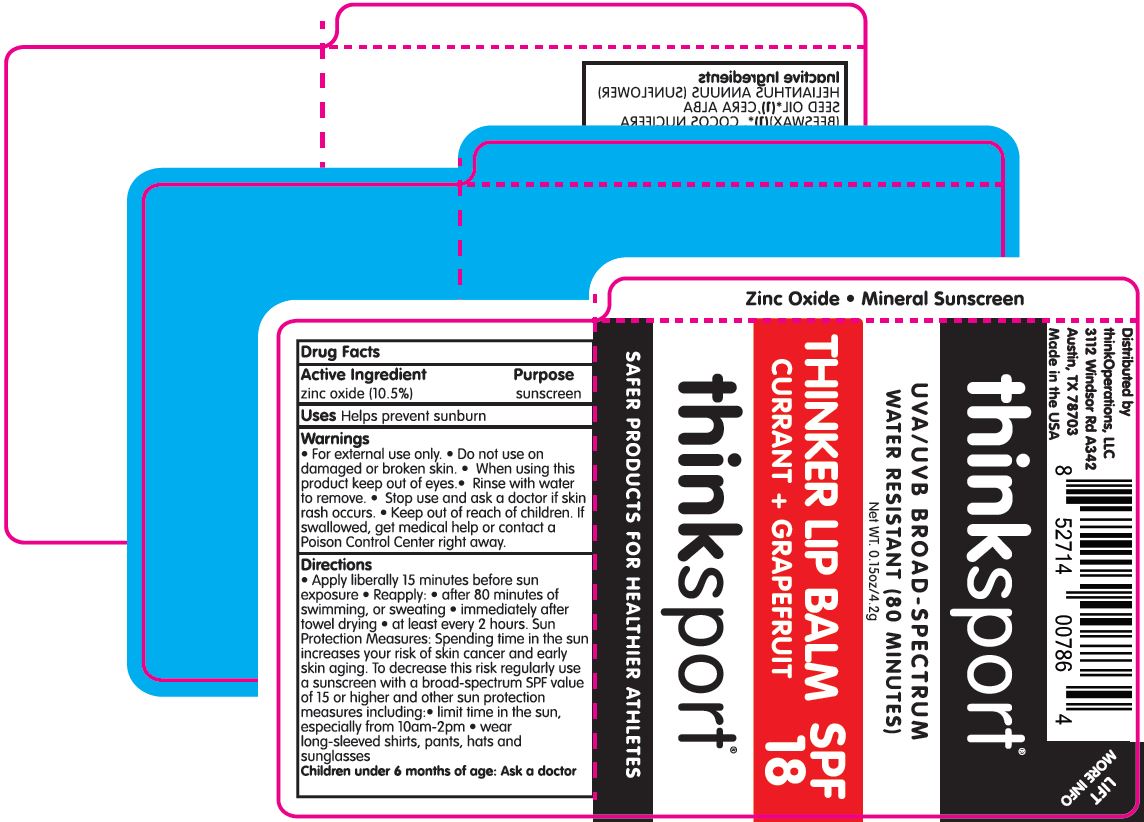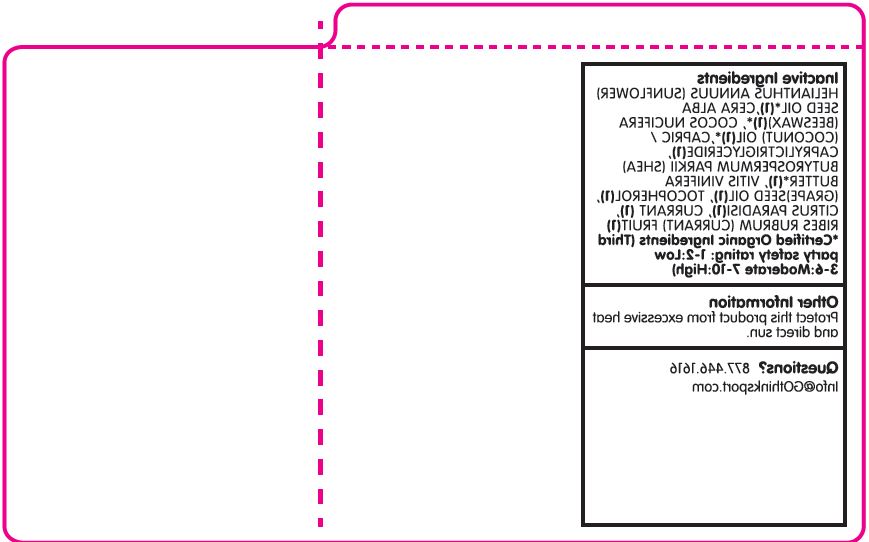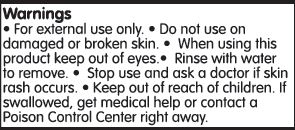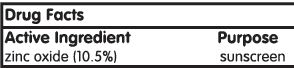 DRUG LABEL: LIP BALM
NDC: 62932-247 | Form: STICK
Manufacturer: Private Label Select Ltd CO
Category: otc | Type: HUMAN OTC DRUG LABEL
Date: 20220104

ACTIVE INGREDIENTS: ZINC OXIDE 10.5 g/100 g
INACTIVE INGREDIENTS: JOJOBA OIL; .BETA.-TOCOPHEROL; RASPBERRY SEED OIL; TAMANU OIL; .ALPHA.-TOCOPHEROL, D-; SUNFLOWER OIL; COCONUT OIL; POLYHYDROXYSTEARIC ACID STEARATE; WHITE WAX; POLYHYDROXYSTEARIC ACID (2300 MW); SHEA BUTTER; COCOA BUTTER; MEDIUM-CHAIN TRIGLYCERIDES; .GAMMA.-TOCOPHEROL; .DELTA.-TOCOPHEROL

Think Operations, ThinkSport Currant + Grapefruit, SPF 18 (Single)